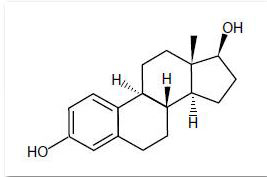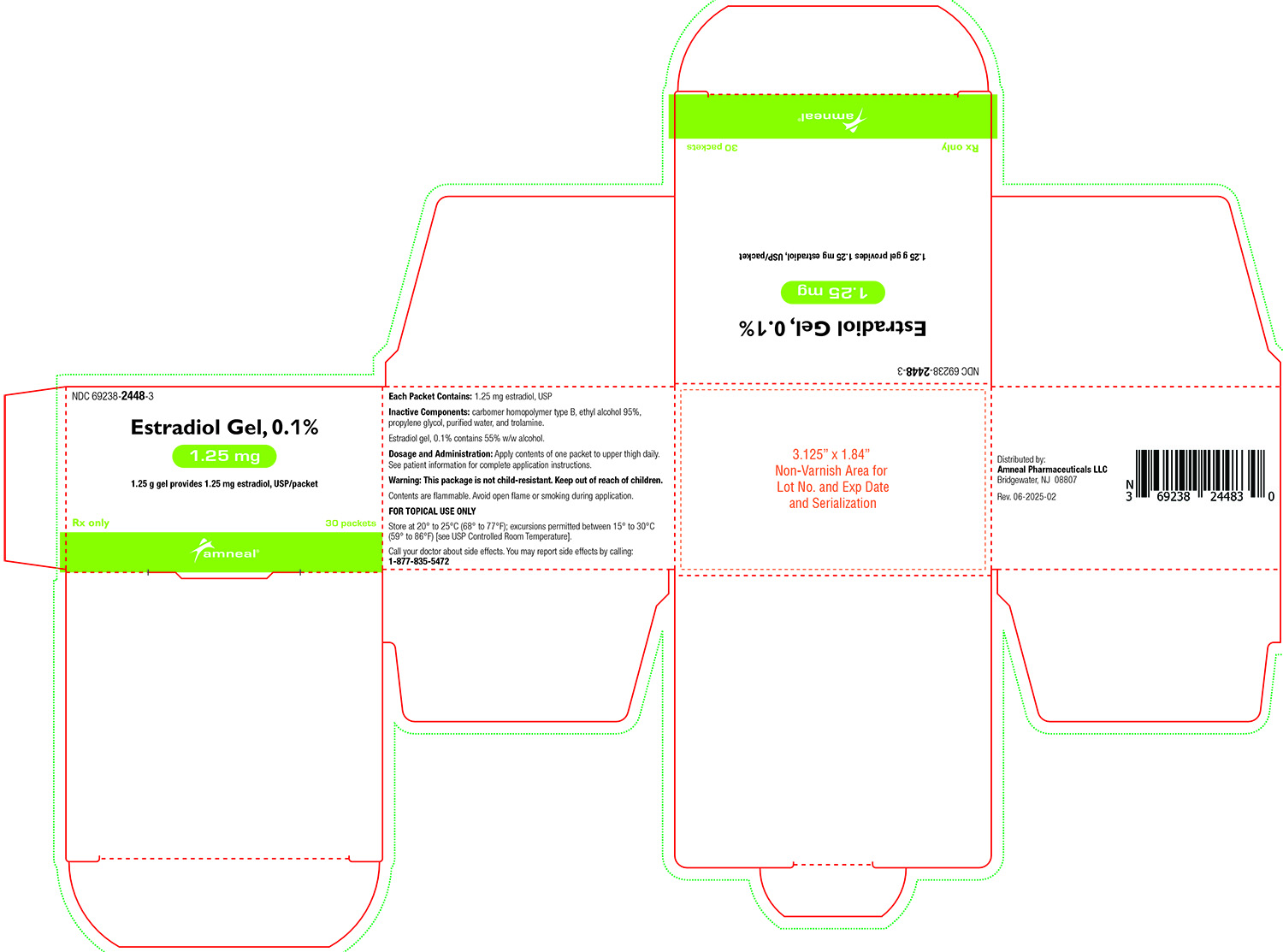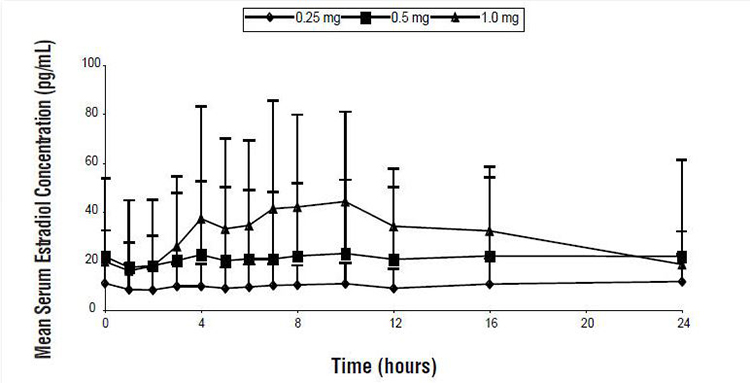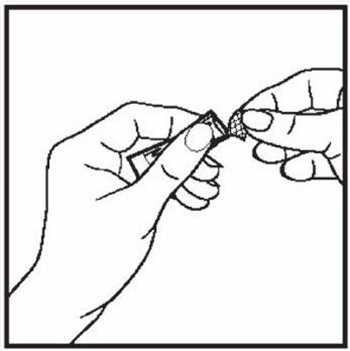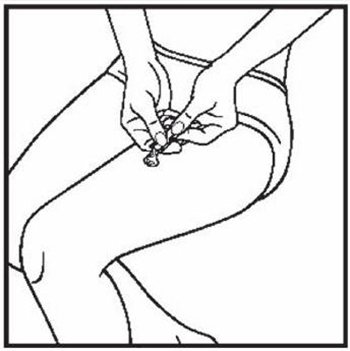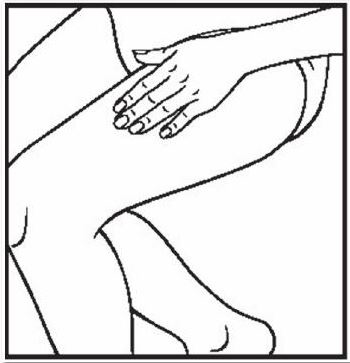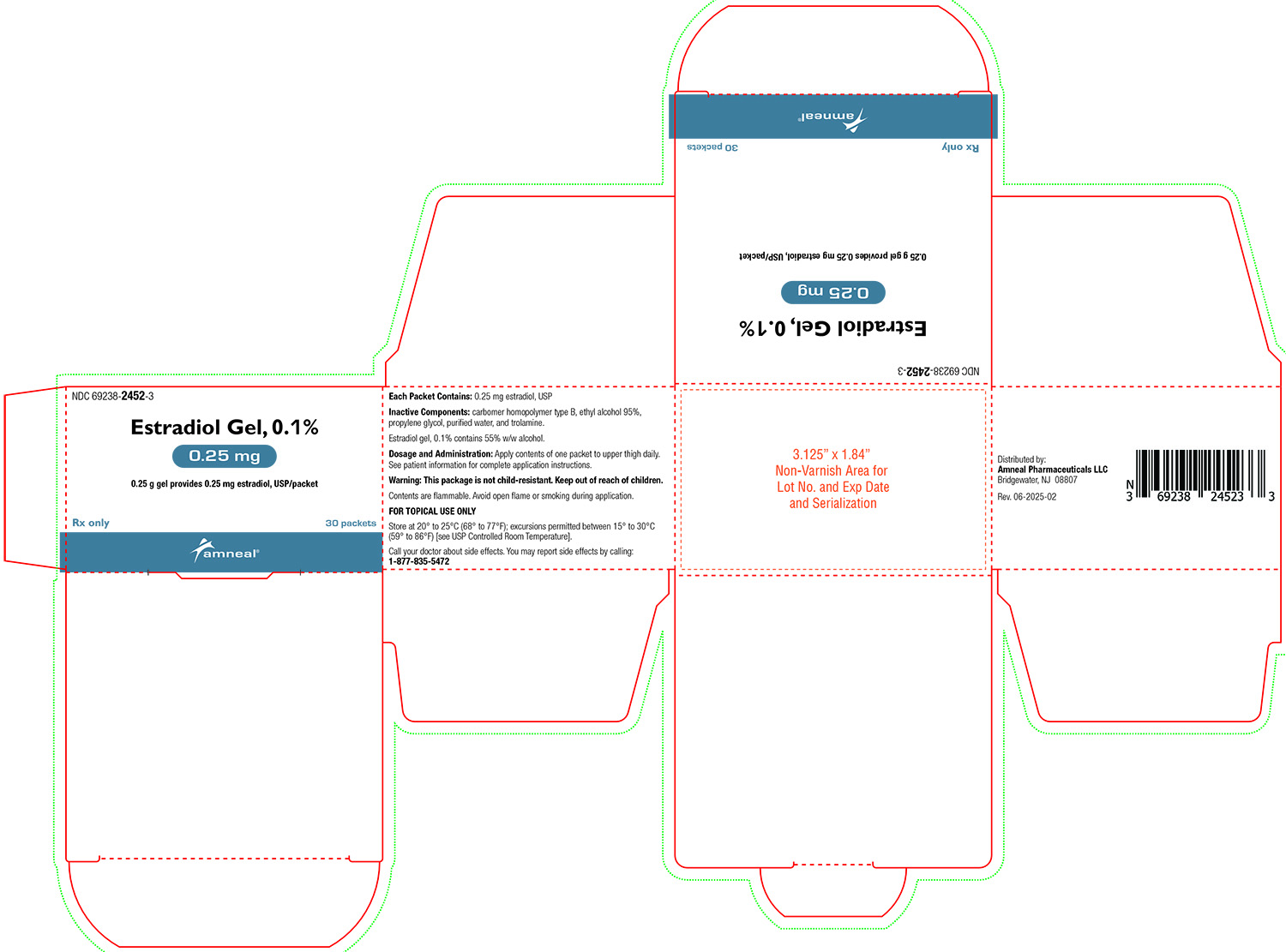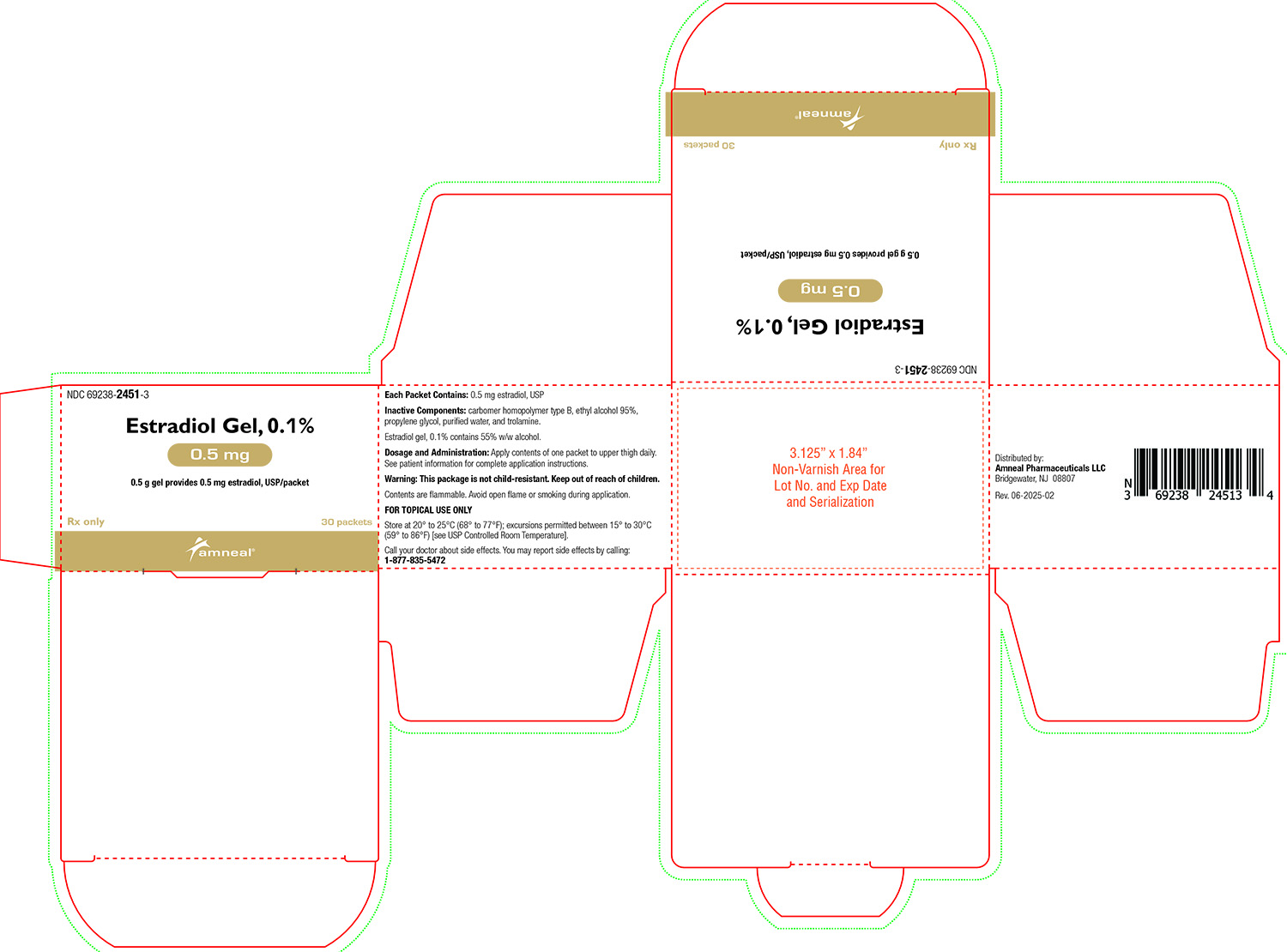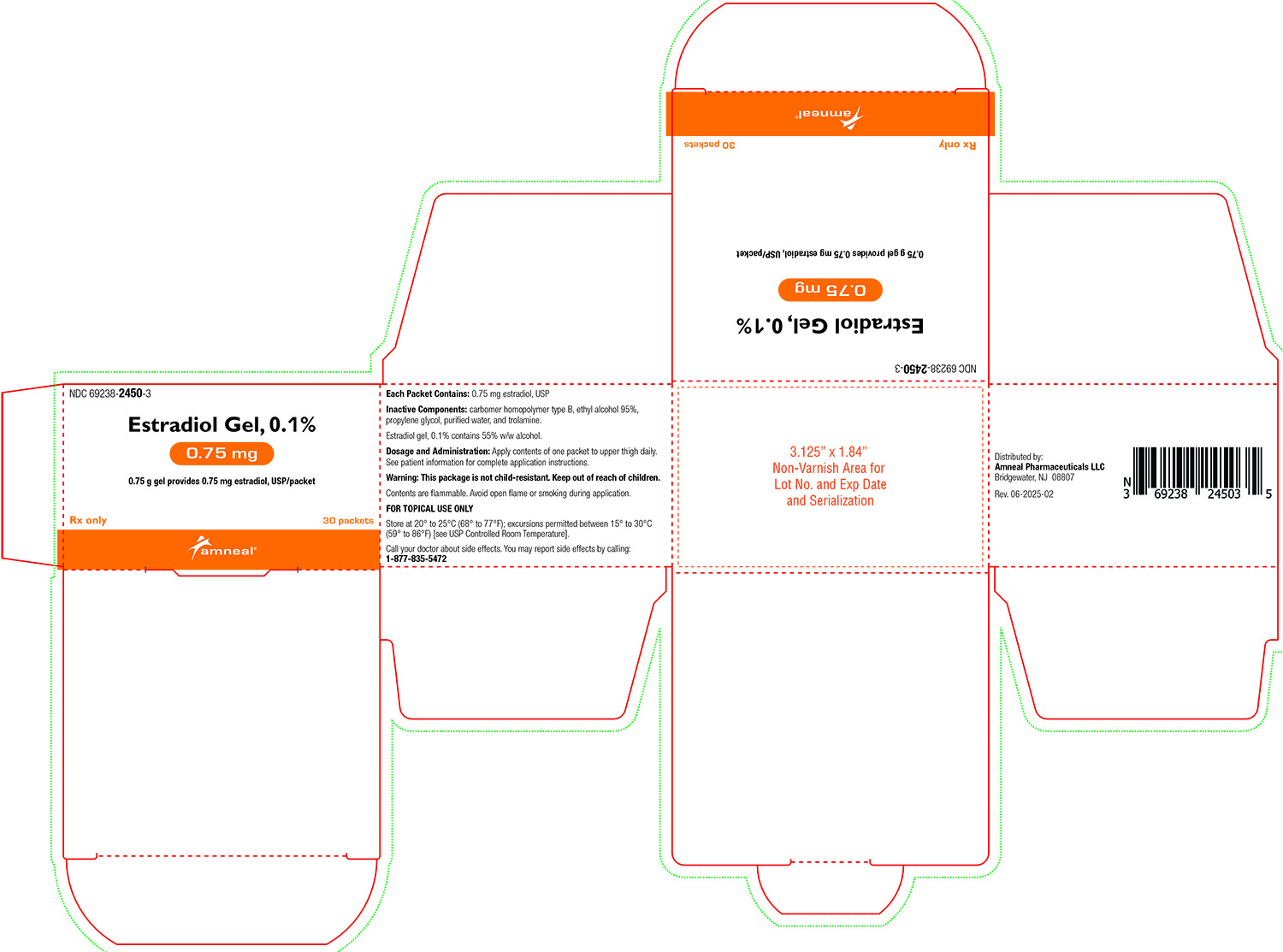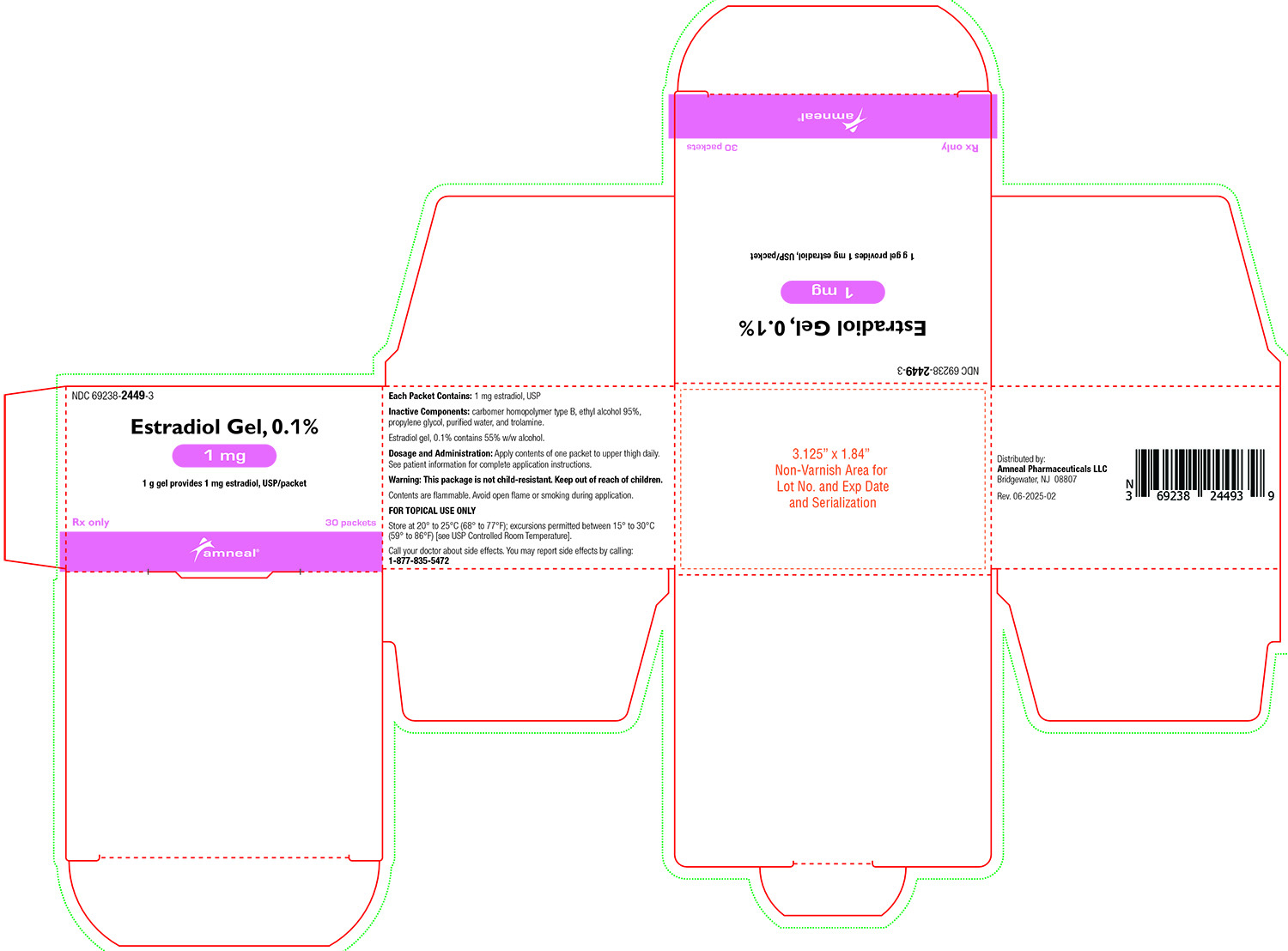 DRUG LABEL: Estradiol
NDC: 69238-2452 | Form: GEL
Manufacturer: Amneal Pharmaceuticals NY LLC
Category: prescription | Type: HUMAN PRESCRIPTION DRUG LABEL
Date: 20260219

ACTIVE INGREDIENTS: ESTRADIOL 0.25 mg/0.25 g
INACTIVE INGREDIENTS: CARBOMER HOMOPOLYMER TYPE B (ALLYL PENTAERYTHRITOL CROSSLINKED); ALCOHOL; PROPYLENE GLYCOL; WATER; TROLAMINE

HIGHLIGHTS OF PRESCRIBING INFORMATION

These highlights do not include all the information needed to use ESTRADIOL GEL safely and effectively. See full prescribing information for ESTRADIOL GEL.
ESTRADIOL gel, for topical use
Initial U.S. Approval: 1975

WARNING: ENDOMETRIAL CANCER WITH UNOPPOSED ESTROGEN IN WOMEN WITH A UTERUS

See full prescribing information for complete boxed warning.

There is an increased risk of endometrial cancer in a woman with a uterus who uses unopposed estrogens (5.2)

RECENT MAJOR CHANGES

Boxed Warning, Cardiovascular Disorders, Breast Cancer, Probable Dementia removed 2/2026
Dosage and Administration, Important Use Information (2.1) 2/2026
Contraindications (4) 2/2026
Warnings and Precautions, Cardiovascular Disorders (5.1) 2/2026
Warnings and Precautions, Malignant Neoplasms (5.2) 2/2026
Warnings and Precautions, Risks Associated with Co-administration of Estrogen Plus Progestogen (5.3) 2/2026
Warnings and Precautions, Probable Dementia removed 2/2026
Warnings and Precautions, Addition of a Progestogen When a Woman Has Not Had a Hysterectomy removed 2/2026

1 INDICATIONS AND USAGE

Estradiol gel, 0.1% is an estrogen indicated for the treatment of moderate to severe vasomotor symptoms due to menopause (1.1).

2 DOSAGE AND ADMINISTRATION

Daily administration of 0.25 to 1.25 grams of estradiol gel, 0.1% to the right or left upper thigh on alternating days. Women should be started with the lowest effective dose and the dose should be evaluated periodically (2).

3 DOSAGE FORMS AND STRENGTHS

Gel: 0.25, 0.5, 0.75, 1, and 1.25 gram-filled single-dose foil packets containing 0.25, 0.5, 0.75, 1, and 1.25 mg estradiol USP, respectively (3)

4 CONTRAINDICATIONS

- Undiagnosed abnormal genital bleeding (4)
- Breast cancer or a history of breast cancer (4, 5.2)
- Estrogen-dependent neoplasia (4, 5.2)
- Active DVT, PE, or history of these conditions (4, 5.1)
- Active arterial thromboembolic disease (e.g., stroke and MI), or history of these conditions (4, 5.1)
- Known anaphylactic reaction, angioedema, or hypersensitivity to estradiol gel (4)
- Hepatic impairment or disease (4, 5.9)
- Protein C, protein S, or antithrombin deficiency, or other known thrombophilic disorders (4)

5 WARNINGS AND PRECAUTIONS

- Cardiovascular Disorders: Increased risk of PE, DVT, and stroke with estrogen-alone therapy. Discontinue if an arterial or venous thrombotic or thromboembolic event occurs. (5.1)
- Estrogens increase the risk of gallbladder disease (5.4)
- Discontinue estrogen if severe hypercalcemia, loss of vision, severe hypertriglyceridemia or cholestatic jaundice occurs (5.5, 5.6, 5.8, 5.9)
- Monitor thyroid function in women on thyroid replacement therapy (5.10, 5.21)

6 ADVERSE REACTIONS

The most common adverse reactions (incidence >5 percent and greater than placebo) in any estradiol gel treatment group are metrorrhagia, breast tenderness, vaginal mycosis, nasopharyngitis, and upper respiratory tract infection (6.1).

To report SUSPECTED ADVERSE REACTIONS, contact Amneal Pharmaceuticals at 1-877-835-5472 or FDA at 1-800-FDA-1088 or www.fda.gov/medwatch.

7 DRUG INTERACTIONS

- Inducers and inhibitors of CYP3A4 may affect estrogen drug metabolism and decrease or increase the estrogen plasma concentration (7).

FULL PRESCRIBING INFORMATION

WARNING: ENDOMETRIAL CANCER WITH UNOPPOSED ESTROGEN IN WOMEN WITH A UTERUS

- There is an increased risk of endometrial cancer in a woman with a uterus who uses unopposed estrogens. Adding a progestogen to estrogen-only therapy has been shown to reduce the risk of endometrial hyperplasia, which may be a precursor to endometrial cancer.
- Perform adequate diagnostic measures, including directed or random endometrial sampling when indicated, to rule out malignancy in menopausal women abnormal genital bleeding of unknown etiology [see Warnings and Precautions (5.2)].

2 DOSAGE AND ADMINISTRATION

2.1 Important Use Information

The timing of estradiol gel, 0.1% initiation can affect the overall benefit-risk profile. Consider initiating estradiol gel, 0.1% in women <60 years old or <10 years since menopause onset [see Warnings and Precautions (5), Use in Specific Populations (8.5) and Clinical Studies (14)].

When estrogen is prescribed for a menopausal woman with a uterus, the addition of a progestogen has been shown to reduce the risk of endometrial cancer. There are possible risks associated with the use of progestogens plus estrogens that differ from those of estrogen-alone regimens. See prescribing information for progestogens indicated for the prevention of endometrial hyperplasia in non-hysterectomized menopausal women receiving estrogens [see Warnings and Precautions (5.2, 5.3)].

Generally, a woman without a uterus, does not need to use a progestogen with estrogen therapy. In some cases, however, hysterectomized women with a history of endometriosis may benefit from the addition of a progestogen [see Warnings and Precautions (5.13)].

2.2 Treatment of Moderate to Severe Vasomotor Symptoms due to Menopause

Start therapy with the 0.25 grams applied once daily on the skin of either the right or left upper thigh. Adjust the dose up to a maximum of 1.25 grams, as needed.

The application surface area should be about 5 by 7 inches (approximately the size of two palm prints). The entire contents of a unit dose packet should be applied each day. To avoid potential skin irritation, apply estradiol gel, 0.1% to the right or left upper thigh on alternating days. Do not apply estradiol gel, 0.1% on the face, breasts, or irritated skin or in or around the vagina. Allow gel to dry after application before dressing. Do not wash the application site within 1 hour after applying estradiol gel, 0.1%. Avoid contact of the gel with eyes. Wash hands after application.

3 DOSAGE FORMS AND STRENGTHS

Estradiol gel, 0.1% is available in five doses of 0.25, 0.5, 0.75, 1, and 1.25 grams for transdermal application (corresponding to 0.25, 0.5, 0.75, 1, and 1.25 mg estradiol USP, respectively). Estradiol gel, 0.1% is a clear, colorless gel, which is odorless when dry.

4 CONTRAINDICATIONS

Estradiol gel is contraindicated in women with any of the following conditions:

- Abnormal genital bleeding of unknown etiology [see Warning and Precautions (5.2)]
- Current or history of breast cancer [see Warning and Precautions (5.2)]
- Estrogen-dependent neoplasia [see Warning and Precautions (5.2)]
- Active DVT, PE, or history of these conditions [see Warning and Precautions (5.1)]
- Active arterial thromboembolic disease (for example, stroke or MI), or a history of these conditions [see Warning and Precautions (5.1)]
- Known anaphylactic reaction, angioedema, or hypersensitivity to estradiol gel
- Hepatic impairment or disease [see Warnings and Precautions (5.9)]
- Protein C, protein S, or antithrombin deficiency, or other known thrombophilic disorders

5 WARNINGS AND PRECAUTIONS

5.1 Cardiovascular Disorders

Estradiol gel is contraindicated in women with active DVT, PE, stroke, or a history of these conditions [see Contraindications (4)]. Immediately discontinue estradiol gel if a PE, DVT, or stroke, occurs or is suspected. If feasible, discontinue estradiol gel at least 4 to 6 weeks before surgery of the type associated with an increased risk of thromboembolism, or during periods of prolonged immobilization.

The safety and efficacy of estradiol gel for the prevention of cardiovascular disorders has not been established.

The Women’s Health Initiate (WHI) estrogen-alone trial reported increased risks of pulmonary embolism (PE), deep vein thrombosis (DVT), and stroke, in postmenopausal women (50 to 79 years of age, average age 63.4 years) during 7.2 years of treatment with daily oral conjugated estrogen (CE) [0.625 mg] relative to placebo. Analyses were also conducted in women aged 50 to 59 years, a group of women more likely to present with onset of moderate to severe VMS compared to women of other age groups in the trial.

Only daily oral 0.625 mg CE was studied in the WHI estrogen-alone trial. Therefore, the relevance of the WHI findings regarding adverse cardiovascular events to lower CE doses, other routes of administration, or other estrogen products is not known. Without such data, it is not possible to definitively exclude these risks or determine the extent of these risks for other products [see Clinical Studies (14.2)].

Venous Thromboembolism

In women aged 50 to 59 years, the WHI estrogen-alone trial reported a relative risk for PE of 1.53 (95% confidence interval [CI], 0.63, 3.75) for CE compared to placebo, with an absolute risk difference of 4 per 10,000 women-years (WYs; 10 versus 6). The relative risk for DVT was 1.66 (95% CI 0.75, 3.67) for CE compared to placebo, with a risk difference of 5 per 10,000 WYs (13 versus 8).

In the overall study population of women aged 50 to 79 years, the WHI estrogen-alone trial reported a relative risk of PE of 1.35 (95% CI 0.89, 2.05) for CE compared to placebo, with a risk difference of 4 per 10,000 WYs (14 versus 10). The relative risk for DVT was 1.48 (95% 1.06, 2.07) for CE compared to placebo, with a risk difference of 7 per 10,000 WYs (23 versus 15) [see Clinical Studies (14.2)].

Stroke

In women aged 50 to 59 years, the WHI estrogen-alone trial reported a relative risk for stroke of 0.99 (95% 0.53, 1.85) for CE compared to placebo, with a risk difference of -1 per 10,000 WYs (16 versus 17).

In the overall study population of women aged 50 to 79 years, the WHI estrogen-alone trial reported a relative risk for stroke of 1.35 (95%, 1.07, 1.70) for CE compared to placebo, with a risk difference of 11 per 10,000 WYs (45 versus 34) [see Clinical Studies (14.2)].

5.2 Malignant Neoplasms

Endometrial Cancer

In estradiol gel-treated menopausal women with a uterus with persistent or recurring abnormal genital bleeding of unknown etiology, perform adequate diagnostic measures, including directed or random endometrial sampling when indicated, to assess for endometrial cancer.

An increased risk of endometrial cancer has been reported with the use of unopposed estrogen therapy in a woman with a uterus. The reported endometrial cancer risk among unopposed estrogen users is about 2 to 12 times greater than in non-users and appears dependent on duration of treatment and on estrogen dose. Most studies show no significant increased risk associated with use of estrogens for less than 1 year. The greatest risk appears to be associated with prolonged use, with increased risks of 15- to 24-fold for 5 to 10 years or more. This risk has been shown to persist for at least 8 to 15 years after estrogen therapy is discontinued. There is no evidence that the use of natural estrogens results in a different endometrial risk profile than synthetic estrogens of equivalent estrogen dose.

Adding a progestogen to estrogen-alone therapy has been shown to reduce the risk of endometrial hyperplasia, which may be a precursor to endometrial cancer. There are, however, possible risks associated with the use of progestogens plus estrogens that differ from those of estrogen-alone regimens [see Warnings and Precautions (5.3)].

Breast Cancer

Surveillance measures for breast cancer, such as breast examinations and mammography, are recommended. The use of estrogen-alone therapy has been reported to result in an increase in abnormal mammograms requiring further evaluation.

In the WHI estrogen-alone trial, after an average follow-up of 7.1 years, daily CE-alone was not associated with an increased risk of invasive breast cancer. Among women 50 to 59 years old, the relative risk was 0.82 (95% CI, 0.50, 1.34) for CE compared to placebo, with a risk difference of -5 per 10,000 WYs (24 versus 29). In the overall study population of women aged 50 to 79 years (average age 63.4 years), the relative risk was 0.79 (95% CI, 0.61, 1.02), with a risk difference of -7 per 10,000 WYs (28 versus 35) [see Clinical Studies (14.2)]. However, a large meta-analysis including 24 prospective studies of postmenopausal women comparing current use of estrogen-only products with use duration of 5 to 14 years (average of 9 years) versus never use reported a relative risk for breast cancer of 1.33 (95% CI, 1.28 to 1.38).^1

Ovarian Cancer

A large meta-analysis including 17 prospective studies of postmenopausal women compared current use of estrogen-only products versus never use and reported a relative risk for ovarian cancer of 1.37 (95% CI, 1.26 to 1.50). The duration of hormone therapy use that was associated with an increased risk of ovarian cancer is unknown.^2

5.3 Risks Associated with the Co-administration of Estrogen Plus Progestogen

Studies of the addition of a progestogen for 10 or more days of a cycle of estrogen administration, or daily with estrogen in a continuous regimen, have reported a lowered incidence of endometrial hyperplasia than would be induced by estrogen treatment alone. Endometrial hyperplasia may be a precursor to endometrial cancer.

If estradiol gel is administered with a progestogen, there are possible risks associated with the use of progestogens plus estrogens that differ from those of estrogen-alone regimens. Refer to prescribing information for progestogens indicated for the prevention of endometrial hyperplasia in non-hysterectomized women receiving estrogens.

5.4 Gallbladder Disease

A 2- to 4-fold increase in the risk of gallbladder disease requiring surgery in postmenopausal women receiving estrogens has been reported.

5.5 Hypercalcemia

Estrogen administration may lead to severe hypercalcemia in women with breast cancer and bone metastases. Discontinue estrogens, including estradiol gel, if hypercalcemia occurs, and take appropriate measures to reduce the serum calcium level.

5.6 Visual Abnormalities

Retinal vascular thrombosis has been reported in patients receiving estrogens. Discontinue estradiol gel pending examination if there is sudden partial or complete loss of vision, or a sudden onset of proptosis, diplopia, or migraine. Permanently discontinue estrogens, including estradiol gel, if examination reveals papilledema or retinal vascular lesions.

5.7 Elevated Blood Pressure

In a small number of case reports, substantial increases in blood pressure have been attributed to idiosyncratic reactions to estrogens. In a large, randomized, placebo-controlled clinical trial, a generalized effect of estrogens on blood pressure was not seen.

5.8 Exacerbation of Hypertriglyceridemia

In women with pre-existing hypertriglyceridemia, estrogen therapy may be associated with elevations of plasma triglycerides leading to pancreatitis. Discontinue estradiol gel if pancreatitis occurs.

5.9 Hepatic Impairment and/or Past History of Cholestatic Jaundice

Estrogens may be poorly metabolized in women with hepatic impairment. Exercise caution in any woman with a history of cholestatic jaundice associated with past estrogen use or with pregnancy. In the case of recurrence of cholestatic jaundice, discontinue estradiol gel.

5.10 Exacerbation of Hypothyroidism

Estrogen administration leads to increased thyroid-binding globulin (TBG) levels. Women with normal thyroid function can compensate for the increased TBG by making more thyroid hormone, thus maintaining free T4 and T3 serum concentrations in the normal range. Women dependent on thyroid hormone replacement therapy who are also receiving estrogens may require increased doses of their thyroid replacement therapy. Monitor thyroid function in these women during treatment with estradiol gel to maintain their free thyroid hormone levels in an acceptable range.

5.11 Fluid Retention

Estrogens may cause some degree of fluid retention. Monitor any woman with a condition(s) that might predispose her to fluid retention, such as a cardiac or renal impairment. Discontinue estrogen-alone therapy, including estradiol gel, with evidence of medically concerning fluid retention.

5.12 Hypocalcemia

Estrogen-induced hypocalcemia may occur in women with hypoparathyroidism. Consider whether the benefits of estrogen therapy outweigh the risks in such women.

5.13 Exacerbation of Endometriosis

A few cases of malignant transformation of residual endometrial implants have been reported in women treated post-hysterectomy with estrogen-alone therapy. Consider the addition of a progestogen therapy for a woman known to have residual endometriosis post-hysterectomy.

5.14 Hereditary Angioedema

Exogenous estrogens may exacerbate symptoms of angioedema in women with hereditary angioedema. Consider whether the benefits of estrogen therapy, including estradiol gel, outweigh the risks in such women.

5.15 Exacerbation of Other Conditions

Estrogen therapy, including estradiol gel, may cause an exacerbation of asthma, diabetes mellitus, epilepsy, migraine, porphyria, systemic lupus erythematosus, and hepatic hemangiomas. Consider whether the benefits of estrogen therapy outweigh the risks in women with such conditions.

5.16 Photosensitivity

The effects of direct sun exposure to estradiol gel application sites have not been evaluated in clinical trials.

5.17 Application of Sunscreen and Topical Solutions

Studies conducted using other approved topical estrogen gel products have shown that sunscreens have the potential for changing the systemic exposure of topically applied estrogen gels.

The effect of sunscreens and other topical lotions on the systemic exposure of estradiol gel has not been evaluated in clinical trials.

5.18 Flammability of Alcohol-Based Gels

Alcohol based gels are flammable. Avoid fire, flame, or smoking until estradiol gel has dried.

Occlusion of the area where the topical drug product is applied with clothing or other barriers is not recommended until estradiol gel has completely dried.

5.19 Potential for Estradiol Transfer and Effects of Washing

There is a potential for drug transfer from one individual to the other following physical contact of estradiol gel application sites. In a study to evaluate transferability to males from their female contacts, there was some elevation of estradiol levels over baseline in the male subjects; however, the degree of transferability in this study was inconclusive. Women are advised to avoid skin contact with other persons until the gel is completely dried. The site of application should be covered (clothed) after drying.

Washing the application site with soap and water 1 hour after application resulted in a 30 to 38 percent decrease in the mean total 24-hour exposure to estradiol. Therefore, women should refrain from washing the application site for at least one hour after application.

5.20 Laboratory Tests

Serum follicle stimulating hormone (FSH) and estradiol levels are not useful in the management of moderate to severe vasomotor symptoms.

5.21 Drug-Laboratory Test Interactions

- Accelerated prothrombin time, partial thromboplastin time, and platelet aggregation time; increased platelet count; increased factors II, VII antigen, VIII antigen, VIII coagulant activity, IX, X, XII, VII-X complex, II-VII-X complex, and beta-thromboglobulin; decreased levels of anti-factor Xa and antithrombin III, decreased antithrombin III activity; increased levels of fibrinogen and fibrinogen activity; increased plasminogen antigen and activity.
- Increased thyroid binding globulin (TBG) levels leading to increased circulating total thyroid hormone levels, as measured by protein-bound iodine (PBI), T4 levels (by column or by radioimmunoassay) or T3 levels by radioimmunoassay. T3 resin uptake is decreased, reflecting the elevated TBG. Free T4 and free T3 concentrations are unaltered. Women on thyroid replacement therapy may require higher doses of thyroid hormone.
- Other binding proteins may be elevated in serum, for example, corticosteroid binding globulin (CBG), sex hormone-binding globulin (SHBG), leading to increased total circulating corticosteroids and sex steroids, respectively. Free hormone concentrations, such as testosterone and estradiol, may be decreased. Other plasma proteins may be increased (angiotensinogen/renin substrate, alpha-l-antitrypsin, ceruloplasmin).
- Increased plasma high-density lipoprotein (HDL) and HDL2 cholesterol subfraction concentrations, reduced low-density lipoprotein (LDL) cholesterol concentration, increased triglyceride levels.
- Impaired glucose tolerance.

6 ADVERSE REACTIONS

The following serious adverse reactions are discussed elsewhere in the labeling:

- Cardiovascular Disorders [see Boxed Warning, Warnings and Precautions (5.1)].
- Malignant Neoplasms [see Boxed Warning, Warnings and Precautions (5.2)].

6.1 Clinical Trials Experience

Because clinical trials are conducted under widely varying conditions, adverse reaction rates observed in the clinical trials of a drug cannot be directly compared to rates in the clinical trials of another drug and may not reflect the rates observed in practice.

Estradiol gel was studied at doses of 0.25, 0.5 and 1 gram per day in a 12-week, double-blind, placebo-controlled study that included a total of 495 postmenopausal women (86.5 percent Caucasian). The adverse reactions that occurred at a rate greater than 5 percent and greater than placebo in any of the treatment groups are summarized in Table 1.

Table 1: Number (%) of Subjects with Common Adverse Reactions* in a 12-Week Placebo-Controlled Study of Estradiol Gel
 | Estradiol Gel |  |  | Placebo
SYSTEM ORGAN CLASS Preferred Term | 0.25 grams/day N=122 n (%) | 0.5 grams/day N=123 n (%) | 1 gram/day N=125 n (%) | N=125 n (%)
INFECTIONS & INFESTATIONS
Nasopharyngitis | 7 (5.7) | 5 (4.1) | 6 (4.8) | 5 (4.0)
Upper Respiratory Tract Infection | 7 (5.7) | 3 (2.4) | 2 (1.6) | 2 (1.6)
Vaginal mycosis | 1 (0.8) | 3 (2.4) | 8 (6.4) | 4 (3.2)
REPRODUCTIVE SYSTEM & BREAST DISORDERS
Breast Tenderness | 3 (2.5) | 7 (5.7) | 11 (8.8) | 2 (1.6)
Metrorrhagia | 5 (4.1) | 7 (5.7) | 12 (9.6) | 2 (1.6)
*Adverse reactions reported by >5 percent of patients in any treatment group.

In a 12-week placebo-controlled study of estradiol gel, application site reactions were seen in <1 percent of participating women.

6.2 Postmarketing Experience

The following adverse reactions have been identified during post-approval use of estradiol gel. Because these reactions are reported voluntarily from a population of uncertain size, it is not always possible to reliably estimate their frequency or establish a causal relationship to drug exposure.

Genitourinary System

Amenorrhea, dysmenorrhea, ovarian cyst, vaginal discharge

Breasts

Gynecomastia

Cardiovascular

Palpitations, ventricular extrasystoles

Gastrointestinal

Flatulence

Skin

Rash pruritic, urticaria

Eyes

Retinal vein occlusion

Central Nervous System

Tremor

Miscellaneous

Arthralgia, application site rash, asthenia, chest discomfort, fatigue, feeling abnormal, heart rate increased, insomnia, malaise, muscle spasms, pain in extremity, weight increased

7 DRUG INTERACTIONS

In vitro and in vivo studies have shown that estrogens are metabolized partially by cytochrome P450 3A4 (CYP3A4). Therefore, inducers or inhibitors of CYP3A4 may affect estrogen drug metabolism. Inducers of CYP3A4, such as St. John's wort (Hypericum perforatum) preparations, phenobarbital, carbamazepine, and rifampin, may reduce plasma concentrations of estrogens, possibly resulting in a decrease in therapeutic effects and/or changes in the uterine bleeding profile. Inhibitors of CYP3A4, such as erythromycin, clarithromycin, ketoconazole, itraconazole, ritonavir, and grapefruit juice, may increase plasma concentrations of estrogens and result in adverse reactions.

8 USE IN SPECIFIC POPULATIONS

8.1 Pregnancy

Risk Summary

Estradiol gel is not indicated for use in pregnant women. There are no data with the use of estradiol gel in pregnant women; however, epidemiologic studies and meta-analyses have not found an increased risk of genital or nongenital birth defects (including cardiac anomalies and limb-reduction defects) following exposure to combined hormonal contraceptives (estrogen and progestins) before conception or during early pregnancy.

In the U.S. general population, the estimated background risk of major birth defects and miscarriage in clinically recognized pregnancies is 2% to 4% and 15% to 20%, respectively.

8.2 Lactation

Risk Summary

Estrogens are present in human milk and can reduce milk production in breast-feeding women. This reduction can occur at any time but is less likely to occur once breast-feeding is well established.

The developmental and health benefits of breastfeeding should be considered along with the mother’s clinical need for estradiol gel and any potential adverse effects on the breastfed child from estradiol gel or from the underlying maternal condition.

8.4 Pediatric Use

Estradiol gel is not indicated for use in pediatric patients. Clinical studies have not been conducted in the pediatric population.

8.5 Geriatric Use

There have not been sufficient numbers of geriatric women involved in clinical studies utilizing estradiol gel to determine whether those over 65 years of age differ from younger subjects in their response to estradiol gel.

The Women’s Health Initiative Studies

In the WHI estrogen-alone trial (daily CE [0.625 mg]-alone versus placebo), there was a higher relative risk of stroke in women greater than 65 years of age [see Clinical Studies (14.2)].

The Women's Health Initiative Memory Study

In the WHIMS ancillary studies of postmenopausal women 65 to 79 years of age, there was an increased risk of probable dementia in women receiving estrogen-alone [see Clinical Studies (14.3)].

Since the trial was conducted in women 65 to 79 years of age, it is unknown whether these findings apply to younger postmenopausal women [see Clinical Studies (14.3)]. The safety and efficacy of estradiol gel for the prevention of dementia has not been established.

10 OVERDOSAGE

Overdosage of estrogen may cause nausea and vomiting, breast tenderness, abdominal pain, drowsiness and fatigue, and withdrawal bleeding in women. Treatment of overdose consists of discontinuation of estradiol gel therapy with institution of appropriate symptomatic care.

11 DESCRIPTION

Estradiol gel 0.1%, is a clear, colorless gel, which is odorless when dry. It is designed to deliver sustained circulating concentrations of estradiol, USP when applied once daily to the skin. The gel is applied to a small area (200 cm^2) of the thigh in a thin layer. Estradiol gel is available in five doses of 0.25, 0.5, 0.75, 1, and 1.25 grams for topical application (corresponding to 0.25, 0.5, 0.75, 1, and 1.25 mg estradiol USP, respectively).

The active component of the topical gel is estradiol USP, an estrogen.

Estradiol, USP is a white crystalline powder, chemically described as estra-1,3,5(10)-triene-3,17ß-diol. It has an empirical formula of C18H24O2 and molecular weight of 272.38. The structural formula is:

The remaining components of the gel (carbomer homopolymer type B, ethyl alcohol 95%, propylene glycol, purified water, and trolamine) are pharmacologically inactive.

Estradiol gel, 0.1% contains 55% w/w alcohol.

12 CLINICAL PHARMACOLOGY

12.1 Mechanism of Action

Endogenous estrogens are largely responsible for the development and maintenance of the female reproductive system and secondary sexual characteristics. Although circulating estrogens exist in a dynamic equilibrium of metabolic interconversions, estradiol is the principal intracellular human estrogen and is substantially more potent than its metabolites, estrone and estriol, at the receptor level.

The primary source of estrogen in normally cycling adult women is the ovarian follicle, which secretes 70 to 500 mcg of estradiol daily, depending on the phase of the menstrual cycle. After menopause, most endogenous estrogen is produced by conversion of androstenedione, which is secreted by the adrenal cortex, to estrone in the peripheral tissues. Thus, estrone and the sulfate conjugated form, estrone sulfate, are the most abundant circulating estrogens in postmenopausal women.

Estrogens act through binding to nuclear receptors in estrogen-responsive tissues. To date, two estrogen receptors have been identified. These vary in proportion from tissue to tissue.

Circulating estrogens modulate the pituitary secretion of the gonadotropins, luteinizing hormone (LH) and FSH, through a negative feedback mechanism. Estrogens act to reduce the elevated levels of these hormones seen in postmenopausal women.

12.2 Pharmacodynamics

Generally, a serum estrogen concentration does not predict an individual woman’s therapeutic response to estradiol gel nor her risk for adverse outcomes. Likewise, exposure comparisons across different estrogen products to infer efficacy or safety for the individual woman may not be valid.

12.3 Pharmacokinetics

Absorption

Estradiol diffuses across intact skin and into the systemic circulation by a passive absorption process, with diffusion across the stratum corneum being the rate-limiting factor.

In a 14-day, Phase 1, multiple-dose study, estradiol gel demonstrated linear and approximately dose-proportional estradiol pharmacokinetics at steady-state for both AUC0-24 and Cmax following once daily dosing to the skin of either the right or left upper thigh (Table 2).

Table 2: Mean (%CV) Pharmacokinetic Parameters for Estradiol (uncorrected for baseline) on Day 14 Following Multiple Daily Doses of Estradiol Gel 0.1%
Parameter (units) | Estradiol Gel 0.25 grams | Estradiol Gel 0.5 grams | Estradiol Gel 1 gram
AUC0-24 (pg•h/mL) | 236 (94) | 504 (149) | 732 (81)
Cmax (pg/mL) | 14.7 (84) | 28.4 (139) | 51.5 (86)
Cavg (pg/mL) | 9.8 (92) | 21 (148) | 30.5 (81)
tmax * (h) | 16 (0, 72) | 10 (0, 72) | 8 (0, 48)
E2:E1 ratio | 0.42 | 0.65 | 0.65
*Median (Min, Max).

Steady-state serum concentration of estradiol are achieved by day 12 following daily application of estradiol gel to the skin of the upper thigh. The mean (SD) serum estradiol levels following once daily dosing at day 14 are shown in Figure 1.

Figure 1: Mean (SD) Serum Estradiol Concentrations (Values Uncorrected for Baseline) on Day 14 Following Multiple Daily Doses of Estradiol Gel 0.1%

The effect of sunscreens and other topical lotions on the systemic exposure of estradiol gel has not been evaluated. Studies conducted using topical estrogen gel approved products have shown that sunscreens have the potential for changing the systemic exposure of topically applied estrogen gels.

Distribution

The distribution of exogenous estrogens is similar to that of endogenous estrogens. Estrogens are widely distributed in the body and are generally found in higher concentrations in the sex hormone target organs. Estrogens circulate in the blood largely bound to SHBG and albumin.

Metabolism

Exogenous estrogens are metabolized in the same manner as endogenous estrogens. Circulating estrogens exist in a dynamic equilibrium of metabolic interconversions. These transformations take place mainly in the liver. Estradiol is converted reversibly to estrone, and both can be converted to estriol, which is a major urinary metabolite. Estrogens also undergo enterohepatic recirculation via sulfate and glucuronide conjugation in the liver, biliary secretion of conjugates into the intestine, and hydrolysis in the intestine followed by reabsorption. In postmenopausal women, a significant proportion of the circulating estrogens exist as sulfate conjugates, especially estrone sulfate, which serves as a circulating reservoir for the formation of more active estrogens.

Although the clinical significance has not been determined, estradiol from estradiol gel does not undergo first pass metabolism and provides estradiol to estrone ratios at steady-state in the range of 0.42 to 0.65.

Excretion

Estradiol, estrone, and estriol are excreted in the urine along with glucuronide and sulfate conjugates. The apparent terminal half-life for estradiol was about 10 hours following administration of estradiol gel.

Potential for Estradiol Transfer

The effect of estradiol transfer was evaluated in healthy postmenopausal women who topically applied 1 gram of estradiol gel (single dose) on one thigh. One and 8 hours after gel application, they engaged in direct thigh-to-arm contact with a partner for 15 minutes. While some elevation of estradiol levels over baseline was seen in the male subjects, the degree of transferability in this study was inconclusive.

Effects of Washing

The effect of application site washing on skin surface levels and serum concentrations of estradiol was determined in 16 healthy postmenopausal women after application of 1 gram of estradiol gel to a 200 cm^2 area on the thigh. Washing the application site with soap and water 1 hour after application removed all detectable amounts of estradiol from the surface of the skin and resulted in a 30 to 38 percent decrease in the mean total 24-hour exposure to estradiol.

13 NONCLINICAL TOXICOLOGY

13.1 Carcinogenesis, Mutagenesis, and Impairment of Fertility

Long-term continuous administration of natural and synthetic estrogens in certain animal species increases the frequency of carcinomas of the breast, uterus, cervix, vagina, testis and liver.

14 CLINICAL STUDIES

14.1 Effects on Vasomotor Symptoms in Postmenopausal Women

A randomized, double-blind, placebo-controlled trial evaluated the efficacy of 12-week treatment with three different daily doses of estradiol gel for vasomotor symptoms in 495 postmenopausal women (86.5 percent White; 10.1 percent Black) between 34 and 89 years of age (mean age 54.6) who had at least 50 moderate to severe hot flushes per week at baseline (2-week period prior to treatment). Women applied placebo, estradiol gel 0.25 grams (0.25 mg estradiol), estradiol gel 0.5 grams (0.5 mg estradiol) or estradiol gel 1 gram (1 mg estradiol) once daily to the thigh. Reductions in both the median daily frequency and the median daily severity of moderate to severe hot flushes were statistically significant for the 0.5 grams per day and the 1 gram per day estradiol gel doses when compared to placebo at week 4. Statistically significant reductions in both the median daily frequency and the median daily severity of moderate to severe hot flushes for the estradiol gel 0.25 grams per day dose when compared to placebo were delayed to week 7. There were statistically significant reductions in median daily frequency and severity of hot flushes for all three estradiol gel doses (0.25 grams per day, 0.5 grams per day and 1 gram per day) compared to placebo at week 12. See Table 3 for results.

Table 3: Summary of Change From Baseline in the Median Daily Frequency and Severity of Hot Flushes During Estradiol Gel Treatment (ITT Population)
 | Estradiol Gel |  |  | Placebo
Evaluation | 0.25 grams/day N=121 | 0.5 grams/day N=119 | 1 gram/day N=124 | N=124
Frequency of Daily Hot Flushes
Baseline Median | 9.72 | 9.24 | 9.64 | 9.32
Median Change: Week 4 p-value† | -5.00 0.132 | -5.73 0.011 | -7.20 <0.001 | -3.63
Median Change: Week 7 p-value† | -6.62 <0.001 | -7.14 <0.001 | -7.71 <0.001 | -4.37
Median Change: Week 12 p-value† | -6.88 <0.001 | -7.29 <0.001 | -8.35 <0.001 | -4.48
Severity of Daily Hot Flushes
Baseline Median | 2.52 | 2.51 | 2.52 | 2.54
Median Change: Week 4 p-value† | -0.07 0.283 | -0.18 <0.001 | -0.47 <0.001 | -0.04
Median Change: Week 7 p-value† | -0.24 <0.001 | -0.46 <0.001 | -1.06 <0.001 | -0.06
Median Change: Week 12 p-value† | -0.33 0.021 | -0.56 0.002 | -1.69 <0.001 | -0.13
†p-values from the van Elteren’s test stratified by pooled center; comparison in median change was significant if p<0.05.

14.2 Women’s Health Initiative Estrogen-Alone Trial

The WHI estrogen-alone trial enrolled predominantly healthy postmenopausal women in trial to assess the risks and benefits of daily oral CE (0.625 mg)-alone compared to placebo in the prevention of certain chronic diseases. The primary endpoint was the incidence of CHD (defined as nonfatal MI, silent MI and CHD death), with invasive breast cancer as the primary adverse outcome. A “global index” included the earliest occurrence of CHD, invasive breast cancer, stroke, PE, colorectal cancer, hip fracture, or death due to other cause. This trial did not evaluate the effects of CE-alone on menopausal symptoms.

The WHI estrogen-alone trial was stopped early because an increased risk of stroke was observed, and it was deemed that no further information would be obtained regarding the risks and benefits of estrogen-alone in predetermined primary endpoints. Centrally adjudicated results for stroke events, after an average follow-up of 7.1 years, reported estrogen-alone increased the risk for ischemic stroke compared to placebo, and this excess risk was present in all subgroups of women examined.

No overall difference for primary CHD events (nonfatal MI, silent MI and CHD death) and invasive breast cancer incidence in women receiving CE-alone compared to placebo was reported in final centrally adjudicated results from the estrogen-alone trial, after an average follow-up of 7.1 years.^3,4

Results of the estrogen-alone trial, which included 10,739 women (average age of 63 years, range 50 to 79; 75.3% White, 15.1% Black, 6.1% Hispanic, 3.6% Other), after an average follow-up of 7.1 years are presented in Table A.

Table A: Relative Risk and Risk Difference Observed in the WHI Estrogen-Alone Trial at an Average of 7.1 Years of Follow-upa
Event | Relative Ratio (95% CI)c | Risk Difference (CE vs placebo/10,000 WYs)
CHD events | 0.94 (0.78 to 1.14) | -3 (55 vs 58)
Non-fatal MI | 0.97 (0.79 to 1.21) | -1 (44 vs 45)
CHD death | 1.00 (0.77 to 1.31) | 0 (29 vs 29)
All Strokes | 1.35 (1.07 to 1.70) | 11 (45 vs 34)
Deep vein thrombosisd | 1.48 (1.06 to 2.07) | 7 (23 vs 15)
Pulmonary embolism | 1.35 (0.89 to 2.05) | 4 (14 vs 10)
Invasive breast cancere | 0.79 (0.61 to 1.02) | -7 (28 vs 35)
Colorectal cancer | 1.15 (0.81 to 1.64) | 2 (17 vs 15)
Hip fracture | 0.67 (0.46 to 0.96) | -6 (13 vs 19)
Vertebral fracturesd | 0.64 (0.44 to 0.93) | -6 (12 vs 18)
Total fracturesd | 0.72 (0.64 to 0.80) | -61 (153 vs 214)
Overall mortalityc,f | 1.03 (0.88 to 1.21) | 3 (80 vs 77)
Global Indexg | 1.03 (0.93 to 1.13) | 4 (208 vs 204)
a Adapted from 2013 WHI trial (CE n=5,310, placebo n=5,429). WHI publications can be viewed at www.nhlbi.nih.gov/whi.
b Results are based on centrally adjudicated data.
c In the WHI studies, hazard ratios were estimated using Cox proportional hazards models comparing treatment to placebo; however, they are described here as relative risks. Nominal confidence intervals unadjusted for multiple looks and multiple comparisons.
d Not included in “global index.”
e Includes metastatic and non-metastatic breast cancer with the exception of in situ cancer.
f All deaths, except from breast or colorectal cancer, definite or probable CHD, PE or cerebrovascular disease.
g A subset of the events was combined in a “global index,” defined as the earliest occurrence of CHD events, invasive breast cancer, stroke, PE, colorectal cancer, hip fracture, or death due to other causes.

Timing of the initiation of estrogen-alone therapy to the start of menopause may affect the overall risk benefit profile. The study results for women 50 to 59 years old in the WHI estrogen-alone trial are shown in Table B.

Table B: Relative Risk and Risk Difference Observed Among Women 50-59 Years of Age in the WHI Estrogen-Alone Trial at an Average of 7.1 Yearsa,b
Event | Relative Ratio (95% CI)c | Risk Difference (CE vs placebo/10,000 WYs)
CHD events | 0.60 (0.35 to 1.04) | -11 (17 vs 28)
Non-fatal MI | 0.55 (0.31 to 1.00) | -11 (14 vs 25)
CHD death | 0.80 (0.32 to 2.04) | -1 (7 vs 8)
All Strokes | 0.99 (0.53 to 1.85) | -1 (16 vs 17)
Deep vein thrombosisd | 1.66 (0.75 to 3.67) | 5 (13 vs 8)
Pulmonary embolism | 1.53 (0.63 to 3.75) | 4 (10 vs 6)
Invasive breast cancere | 0.82 (0.50 to 1.34) | -5 (24 vs 29)
Colorectal cancer | 0.71 (0.30 to 1.67) | -3 (7 vs 10)
Hip fracture | 5.01 (0.59 to 42.91) | 3 (1 vs 3)
Vertebral fracturesd | 0.50 (0.17 to 1.47) | -4 (4 vs 8)
Total fracturesd | 0.90 (0.72 to 1.11) | -16 (133 vs 149)
Overall mortalityc,f | 0.70 (0.46 to 1.09) | -11 (29 vs 40)
Global Indexg | 0.84 (0.66 to 1.07) | -19 (98 vs 117)
a Adapted from 2013 WHI trial (CE n=1,639, placebo n=1,674). WHI publications can be viewed at www.nhlbi.nih.gov/whi.
b Results are based on centrally adjudicated data.
c In the WHI studies, hazard ratios were estimated using Cox proportional hazards models comparing treatment to placebo; however, they are described here as relative risks. Nominal confidence intervals unadjusted for multiple looks and multiple comparisons.
d Not included in “global index.”
e Includes metastatic and non-metastatic breast cancer with the exception of in situ cancer.
f All deaths, except from breast or colorectal cancer, definite or probable CHD, PE or cerebrovascular disease.
g A subset of the events was combined in a “global index,” defined as the earliest occurrence of CHD events, invasive breast cancer, stroke, PE, colorectal cancer, hip fracture, or death due to other causes.

14.3 Women’s Health Initiative Memory Study

The WHIMS estrogen-alone ancillary study of WHI enrolled 2,947 predominantly healthy hysterectomized postmenopausal women 65 to 79 years of age (45% were 65 to 69 years of age, 36% were 70 to 74 years of age, and 19% were 75 years of age and older) to evaluate the effects of daily CE (0.625 mg)-alone on the incidence of probable dementia (primary outcome) compared to placebo. Probable dementia as defined in this study included Alzheimer’s disease (AD), vascular dementia (VaD) and mixed type (having features of both AD and VaD). The most common classification of probable dementia in the treatment group and the placebo group was AD.

After an average follow-up of 5.2 years, the relative risk of probable dementia for CE-alone versus placebo was 1.49 (95% CI, 0.83 to 2.66). The absolute risk of probable dementia for CE-alone versus placebo was 37 versus 25 cases per 10,000 women-years. Since the ancillary study was conducted in women 65 to 79 years of age, it is unknown whether these findings apply to younger postmenopausal women [see Warnings and Precautions (5.3) and Use in Specific Populations (8.5)].^5

15 REFERENCES

1. Lancet. Collaborative Group on Hormonal Factors in Breast Cancer. Type and timing of menopausal hormone therapy and breast cancer risk: individual participant meta-analysis of the worldwide epidemiological evidence. 2019 Sep 28;394(10204):1159-1168.
2. Beral V, Gaitskell K, Hermon C, Moser K, Reeves G, Peto R. Collaborative Group On Epidemiological Studies Of Ovarian Cancer; Menopausal hormone use and ovarian cancer risk: individual participant meta-analysis of 52 epidemiological studies. Lancet. 2015 May 9;385(9980):1835-42.
3. Anderson GL, et al; Women's Health Initiative Steering Committee. Effects of conjugated equine estrogen in postmenopausal women with hysterectomy: the Women's Health Initiative randomized controlled trial. JAMA. 2004 Apr 14;291(14):1701-12.
4. Manson, J. E., et al Menopausal hormone therapy and health outcomes during the intervention and extended post stopping phases of the Women's Health Initiative randomized trials. JAMA, 310(13): 1353–1368 (2013).
5. Espeland MA, Rapp SR, Shumaker SA, Brunner R, Manson JE, Sherwin BB, Hsia J, Margolis KL, Hogan PE, Wallace R, Dailey M, Freeman R, Hays J; Women's Health Initiative Memory Study. Conjugated equine estrogens and global cognitive function in postmenopausal women: Women's Health Initiative Memory Study. JAMA. 2004 Jun 23;291(24):2959-68.

16 HOW SUPPLIED/STORAGE AND HANDLING

16.1 How Supplied

Estradiol gel, 0.1% is a clear, colorless, smooth, opalescent gel free from lumps and foreign matter filled in single-dose foil packets of 0.25, 0.5, 0.75, 1, and 1.25 grams, corresponding to 0.25, 0.5, 0.75, 1, and 1.25 mg estradiol USP, respectively.

NDC 69238-2452-3, carton of 30 packets, 0.25 mg estradiol, USP per single-dose foil packet
NDC 69238-2451-3, carton of 30 packets, 0.5 mg estradiol, USP per single-dose foil packet
NDC 69238-2450-3, carton of 30 packets, 0.75 mg estradiol, USP per single-dose foil packet
NDC 69238-2449-3, carton of 30 packets, 1 mg estradiol, USP per single-dose foil packet
NDC 69238-2448-3, carton of 30 packets, 1.25 mg estradiol, USP per single-dose foil packet

Keep out of the reach of children.

16.2 Storage and Handling

Store at 20° to 25°C (68° to 77°F); excursions permitted between 15° to 30°C (59° to 86°F) [see USP Controlled Room Temperature.]

17 PATIENT COUNSELING INFORMATION

Advise women to read the FDA-Approved patient labeling (Patient Information and Instructions for Use).

Vaginal Bleeding

Inform postmenopausal women to report any vaginal bleeding to their healthcare provider as soon as possible [see Warnings and Precautions (5.2)].

Unintentional Secondary Exposure to Estradiol Gel

Inform women about the possibility of secondary exposure to estradiol gel:

- Apply estradiol gel as directed and keep children from contacting exposed application site(s). If direct contact with the application site occurs, wash the contact area thoroughly with soap and water.
- Look for signs of unexpected sexual development, such as breast mass or increased breast size in prepubertal children.
- If signs of unintentional secondary exposure are noticed:

- Have the child(ren) evaluated by a healthcare provider.
- Have women contact their healthcare provider to discuss the appropriate use and handling of estradiol gel when around children.

- Pets may also be unintentionally exposed to estradiol gel if above precautions are not followed.

Possible Serious Adverse Reactions with Estrogen-Alone Therapy

Inform postmenopausal women of possible serious adverse reactions of estrogen-alone therapy including Cardiovascular Disorders and Malignant Neoplasms [see Warnings and Precautions (5.1, 5.2)].

Possible Less Serious but Common Adverse Reactions with Estrogen-Alone Therapy

Inform postmenopausal women of possible less serious but common adverse reactions of estrogen-alone therapy such as headaches, breast pain and tenderness, nausea and vomiting.

Distributed by:
Amneal Pharmaceuticals LLC
Bridgewater, NJ 08807

Rev. 02-2026-05

PATIENT INFORMATION

Estradiol (es” tra dye’ ol) Gel, 0.1%

Read this Patient Information leaflet before you start using estradiol gel, 0.1% and each time you get a refill. There may be new information. This information does not take the place of talking to your healthcare provider about your menopausal symptoms or your treatment.

WHAT IS THE MOST IMPORTANT INFORMATION I SHOULD KNOW ABOUT ESTRADIOL GEL, 0.1% (AN ESTROGEN HORMONE)?

- Using estrogen-alone increases your chance of getting cancer of the uterus (womb).
- Report any unusual vaginal bleeding right away while you are using estradiol gel, 0.1%. Vaginal bleeding after menopause may be a warning sign of cancer of the uterus (womb). Your healthcare provider should check any unusual vaginal bleeding to find out the cause.
- Do not use estrogen-alone to prevent heart disease, heart attacks, strokes or dementia (decline of brain function)
- Using estrogen-alone may increase your chances of getting strokes or blood clots
- Only one estrogen-alone product and dose have been shown to increase your chances of getting strokes, blood clots, and dementia.

Because other products and doses have not been studied in the same way, it is not known how the use of estradiol gel, 0.1% will affect your chances of these conditions. You and your healthcare provider should talk regularly about whether you still need treatment with estradiol gel, 0.1%.

What is estradiol gel, 0.1%?

Estradiol gel, 0.1% is a prescription medicine that contains estradiol (an estrogen hormone). Estradiol gel, 0.1% is a clear, colorless, smooth gel that is odorless when dry. When applied to the skin, estradiol is absorbed through the skin into the bloodstream.

What is estradiol gel, 0.1% used for?

Estradiol gel, 0.1% is used after menopause to:

- Reduce moderate to severe hot flashes
  Estrogens are hormones made by a woman's ovaries. The ovaries normally stop making estrogens when a woman is between 45 to 55 years old. This drop in body estrogen levels causes the "change of life" or menopause (the end of monthly menstrual periods). Sometimes, both ovaries are removed during an operation before natural menopause takes place. The sudden drop in estrogen levels causes "surgical menopause."
  When the estrogen levels begin dropping, some women develop very uncomfortable symptoms, such as feelings of warmth in the face, neck, and chest, or sudden intense feelings of heat and sweating ("hot flashes" or "hot flushes"). In some women, the symptoms are mild, and they will not need estrogens. In other women, symptoms can be more severe.
  Who should not use estradiol gel, 0.1%?
  Do not start using estradiol gel, 0.1% if you:
  - have any unusual vaginal bleeding
    Vaginal bleeding after menopause may be a warning sign of cancer of the uterus (womb). Your healthcare provider should check any unusual vaginal bleeding to find out the cause.
  - have been diagnosed with a bleeding disorder
  - currently have or have had certain cancers
    Estrogens may increase the chances of getting certain types of cancers, including cancer of the breast or uterus (womb). If you have or have had cancer, talk with your healthcare provider about whether you should use estradiol gel, 0.1%.
  - had a stroke or heart attack
  - currently have or have had blood clots
  - currently have or have had liver problems
  - are allergic to estradiol gel, 0.1% or any of its ingredients
  See the list of ingredients in estradiol gel, 0.1% at the end of this leaflet.
  Before you use estradiol gel, 0.1%, tell your healthcare provider about all of your medical conditions, including if you:
  - have any unusual vaginal bleeding
    Vaginal bleeding after menopause may be a warning sign of cancer of the uterus (womb). Your healthcare provider should check any unusual vaginal bleeding to find out the cause.
  - have any other medical conditions that may become worse while you are using estradiol gel, 0.1%
    Your healthcare provider may need to check you more carefully if you have certain conditions, such as asthma (wheezing), epilepsy (seizures), diabetes, migraines, endometriosis, lupus, angioedema (swelling of face and tongue), problems with your heart, liver, thyroid, kidneys, or have high calcium levels in your blood.
  - are going to have surgery or will be on bedrest
    Your healthcare provider will let you know if you need to stop using estradiol gel, 0.1%.
  - are pregnant or think you may be pregnant
    Estradiol gel, 0.1% is not for pregnant women.
  - are breastfeeding
  The hormone in estradiol gel, 0.1% can pass into your breast milk.
  Tell your healthcare provider about all the medicines you take, including prescription and over-the-counter medicines, vitamins, and herbal supplements. Some medicines may affect how estradiol gel, 0.1% works. Estradiol gel, 0.1% may also affect how your other medicines work. Keep a list of your medicines and show it to your healthcare provider and pharmacist when you get new medicine.
  How should I use estradiol gel, 0.1%?
- Take the dose recommended by your healthcare provider and talk to him or her about how well that dose is working for you.
- Estrogens should be used at the lowest dose possible for your treatment and only as long as needed.

You and your healthcare provider should talk regularly (for example, every 3 to 6 months) about the dose you are using and whether you still need treatment with estradiol gel, 0.1%.

How should estradiol gel, 0.1% be applied?

- Estradiol gel, 0.1% should be applied 1-time a day, around the same time each day.
- Apply estradiol gel, 0.1% to clean, dry, and unbroken (without cuts or scrapes) skin. If you take a bath or shower, be sure to apply your estradiol gel, 0.1% after your skin is dry. The application site should be completely dry before dressing or swimming.
- Apply estradiol gel, 0.1% to either your left or right upper thigh. Change between your left and right upper thigh each day to help prevent skin irritation.

TO APPLY:

Step 1: Wash and dry your hands thoroughly.

Step 2: Sit in a comfortable position.

Step 3: Cut or tear the estradiol gel, 0.1% packet as shown in Figure A.

Figure A

Step 4: Using your thumb and pointer (index) finger, squeeze the entire contents of the estradiol gel, 0.1% packet onto the skin of the upper thigh as shown in Figure B.

Figure B

Step 5: Gently spread the gel in a thin layer on your upper thigh over an area of about 5 by 7 inches, or two palm prints as shown in Figure C. It is not necessary to massage or rub in estradiol gel, 0.1%.

Figure C

Step 6: Allow the gel to dry completely before dressing.

Step 7: Throw away (dispose) of the empty estradiol gel, 0.1% packet in the trash.

Step 8: Wash your hands with soap and water immediately after applying estradiol gel, 0.1% to remove any remaining gel and reduce the chance of transferring estradiol gel, 0.1% to other people.

Important things to remember when using estradiol gel, 0.1%

- Allow the gel to dry before dressing. Try to keep the area dry for as long as possible.
- Do not allow another person to come in contact with the area of skin where you applied the gel for at least 1 hour after you apply estradiol gel, 0.1%.
- You should not have another person apply the gel for you. However, if you need to have another person help you, have that person wear a disposable plastic glove to avoid direct contact with estradiol gel, 0.1%.
- Do not apply estradiol gel, 0.1% to your face, breast, or irritated skin.
- Never apply estradiol gel, 0.1% in or around the vagina.
- Estradiol gel, 0.1% contains alcohol. Alcohol based gels are flammable. Avoid fire, flame or smoking until the gel has dried.

What should I do if I miss a dose?

If you miss a dose, do not double the dose on the next day to catch up. If your next dose is less than 12 hours away, it is best just to wait and apply your normal dose the next day. If it is more than 12 hours until the next dose, apply the dose you missed and resume your normal dosing the next day. Do not apply estradiol gel, 0.1% more than 1-time each day. If you accidentally spill some of the contents of an estradiol gel, 0.1% packet, do not open a new estradiol gel, 0.1% packet. Wait and apply your normal dose the next day.

What should I do if someone else is exposed to estradiol gel, 0.1%?

To reduce the chance of transfer to another person (or pet) let the estradiol gel, 0.1% dry completely. Wash your hands with soap and water after application. If someone else is exposed to estradiol gel, 0.1% by direct contact with the wet gel, have that person wash the area of contact with soap and water right away. This is especially important for men and children. The longer the gel is in contact with the skin before washing, the greater the chance that the other person (or pet) will absorb some of the estrogen hormone. This may harm them. In case of any signs or symptoms of estrogen exposure in the other person (or pet), contact your healthcare provider (or veterinarian, if appropriate).

What should I do if I get estradiol gel, 0.1% in my eyes?

If you get estradiol gel, 0.1% in your eyes, flush your eyes right away with lukewarm tap water. If you have concerns, contact your healthcare provider.

What are the possible side effects of estradiol gel, 0.1%?

Side effects are grouped by how serious they are and how often they happen when you are treated.

Serious, but less common side effects include:

- heart attack
- stroke
- blood clots
- breast cancer
- cancer of the lining of the uterus (womb)
- cancer of the ovary
- dementia
- high or low blood calcium (hypercalcemia)
- gall bladder disease
- visual abnormalities
- high blood pressure
- high levels of fat (triglycerides) in your blood
- liver problems
- changes in your thyroid hormone levels
- fluid retention
- cancer change of endometriosis
- enlargement of benign tumors of the uterus (“fibroids”)
- worsening swelling of face and tongue (angioedema)
- changes in certain laboratory test results such as high blood sugar

Call your healthcare provider right away if you get any of the following warning signs or any other unusual symptoms that concern you:

- new breast lumps
- unusual vaginal bleeding
- changes in vision or speech
- sudden new severe headaches
- severe pains in your chest or legs with or without shortness of breath, weakness, and fatigue
- swelling of face, lips, and tongue with or without red, itchy bumps

The most common side effects of estradiol gel, 0.1% include:

- irregular vaginal bleeding or spotting
- breast tenderness
- vaginal yeast infection
- upper respiratory tract (nose, sinuses, pharynx or larynx) infection

These are not all the possible side effects of estradiol gel, 0.1%. For more information, ask your healthcare provider or pharmacist for advice about side effects. Tell your healthcare provider if you have any side effects that bother you or do not go away.

You may report side effects to FDA at 1-800-FDA-1088 or Amneal Pharmaceuticals at 1-877-835-5472.

What can I do to lower my chances of a serious side effect with estradiol gel, 0.1%?

- Talk with your healthcare provider regularly about whether you should continue using estradiol gel, 0.1%.
- If you have a uterus, talk to your healthcare provider about whether the addition of a progestogen is right for you.
- See your healthcare provider right away if you get vaginal bleeding while using estradiol gel, 0.1%.
- Have a pelvic exam, breast exam and mammogram (breast X-ray) every year unless your healthcare provider tells you something else.
- If members of your family have had breast cancer or if you have ever had breast lumps or an abnormal mammogram, you may need to have breast exams more often.
- If you have high blood pressure, high cholesterol (fat in the blood), diabetes, are overweight, or if you use tobacco, you may have higher chances of getting heart disease.

Ask your healthcare provider for ways to lower your chances of getting heart disease.

How should I store estradiol gel, 0.1%?

Store estradiol gel, 0.1% packets at room temperature, 68° to 77°F (20° to 25°C).

Keep estradiol gel, 0.1% and all medicines out of the reach of children.

General information about safe and effective use of estradiol gel, 0.1%

Medicines are sometimes prescribed for purposes other than those listed in a Patient Information leaflet. Do not use estradiol gel, 0.1% for a condition for which it was not prescribed. Do not give estradiol gel, 0.1% to other people, even if they have the same symptoms that you have. It may harm them.

This leaflet provides a summary of the most important information about estradiol gel, 0.1%. If you would like more information, talk with your healthcare provider or pharmacist. You can ask your healthcare provider or pharmacist for information about estradiol gel, 0.1% that is written for health professionals.

What are the ingredients in estradiol gel, 0.1%?

Active ingredient: estradiol, USP.

Inactive ingredients: carbomer homopolymer type B, ethyl alcohol 95%, propylene glycol, purified water, and trolamine.

Contains: 55% alcohol.

How is estradiol gel, 0.1% supplied?

Estradiol gel, 0.1% is supplied in individual foil packets, each one containing a single day's dose.

This Patient Information has been approved by the U.S. Food and Drug Administration.

Distributed by:
Amneal Pharmaceuticals LLC
Bridgewater, NJ 08807

Rev. 02-2026-05